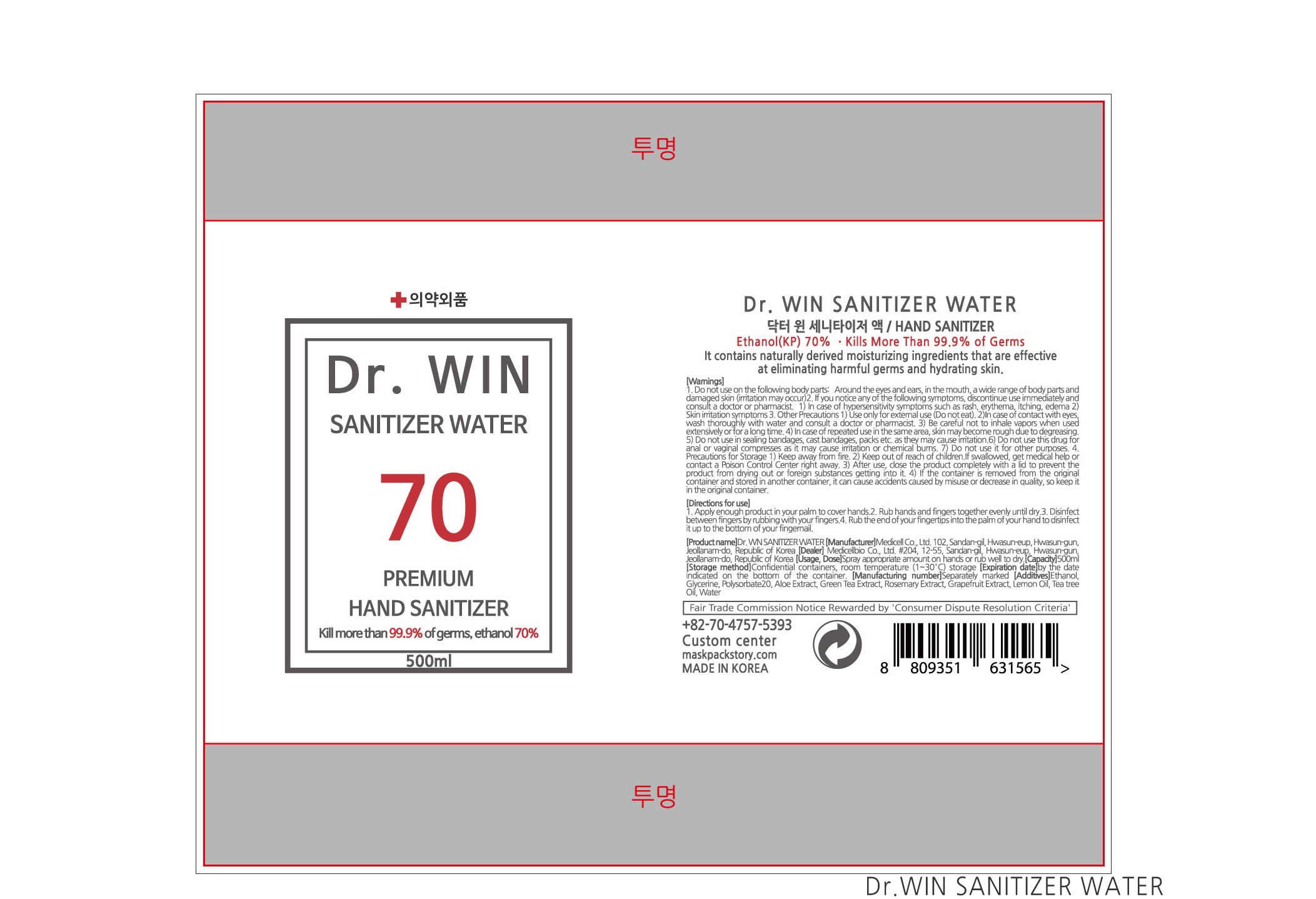 DRUG LABEL: Dr. Win Sanitizer Water
NDC: 75332-0013 | Form: LIQUID
Manufacturer: MEDICELL CO.,LTD
Category: otc | Type: HUMAN OTC DRUG LABEL
Date: 20200705

ACTIVE INGREDIENTS: ALCOHOL 70 mL/100 mL
INACTIVE INGREDIENTS: GREEN TEA LEAF; GLYCERIN; GRAPEFRUIT PEEL; ROSEMARY OIL; LEMON OIL; ALOE VERA LEAF; POLYSORBATE 20; WATER

Drug Facts

ACTIVE INGREDIENT

alcohol

INACTIVE INGREDIENT

Glycerine, Polysorbate20, Aloe Extract, Green Tea Extract, Rosemary Extract, Grapefruit Extract, Lemon Oil, Water

PURPOSE

Sterilization of hands and skin

KEEP OUT OF REACH OF THE CHILDREN

INDICATIONS AND USAGE

Spray appropriate amount on hands and rub well to dry

Gently rubbing thoroughly over all surfaces of both hands.

Dry both hands completely. Be careful not to get into your eyes and mouth when using.

WARNINGS

■ Flammable. Keep away from fire or flame.

■ For external use only.

■ Do not use in eyes.

■ lf swallowed, get medical help promptly.

■ Stop use, ask doctor lf irritation occurs.

■ Keep out of reach of children.

DOSAGE AND ADMINISTRATION

for external use only